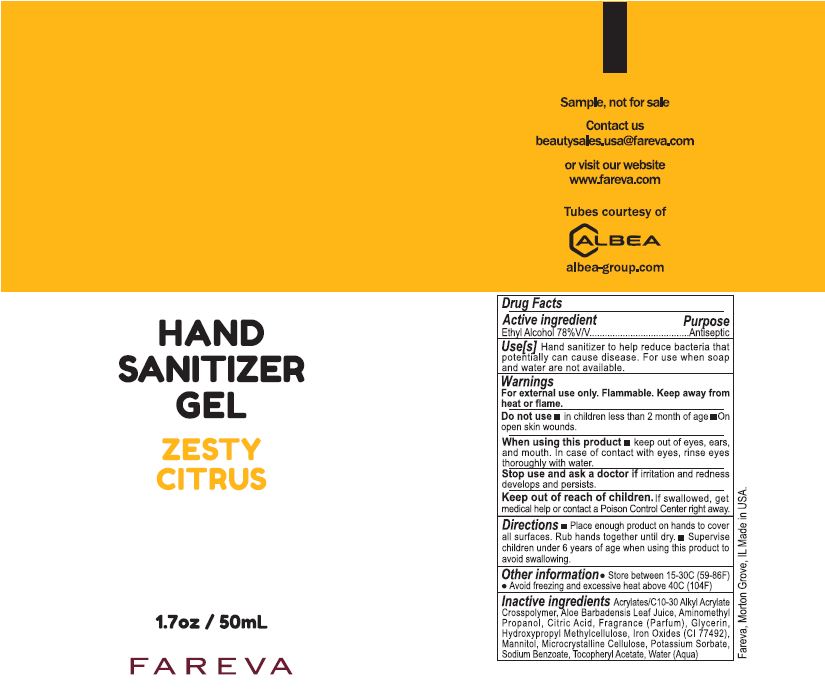 DRUG LABEL: Hand Sanitizer
NDC: 72686-190 | Form: GEL
Manufacturer: Fareva Morton Grove, Inc.
Category: otc | Type: HUMAN OTC DRUG LABEL
Date: 20210222

ACTIVE INGREDIENTS: ALCOHOL 77 mL/100 mL
INACTIVE INGREDIENTS: MICROCRYSTALLINE CELLULOSE; ALPHA-TOCOPHEROL ACETATE; FERRIC OXIDE YELLOW; HYPROMELLOSES; POTASSIUM SORBATE; CARBOMER INTERPOLYMER TYPE A (55000 CPS); MANNITOL; AMINOMETHYLPROPANOL; CITRIC ACID MONOHYDRATE; SODIUM BENZOATE; ALOE VERA LEAF; GLYCERIN; FRAGRANCE LEMON ORC2001060; WATER

HAND SANITIZER GEL ZESTY CITRUS

This is a hand sanitizer manufactured according to the Temporary Policy for Preparation of Certain Alcohol-Based Hand Sanitizer Products During the Public Health Emergency (CoViD-19); Guidance for Industry.

1. Alcohol (ethanol) (USP or Food Chemical Codex (FCC) grade) (77%, volume/volume (v/v)) in an aqueous solution denatured according to Alcohol and Tobacco Tax and Trade Bureau regulations in 27 CFR part 20
2. WATER (AQUA)
3. GLYCERIN
4. FRAGRANCE (PARFUM)
5. ACRYLATES/C10-30 ALKYL ACRYLATE CROSSPOLYMER
6. MANNITOL
7. ALOE BARBADENSIS LEAF JUICE
8. AMINOMETHYL PROPANOL
9. MICROCRYSTALLINE CELLULOSE
10. TOCOPHERYL ACETATE
11. IRON OXIDES (CI 77492)
12. HYDROXYPROPYL METHYLCELLULOSE
13. CITRIC ACID
14. SODIUM BENZOATE
15. POTASSIUM SORBATE

Active Ingredient(s)

Alcohol 77% v/v. Purpose: Antiseptic

Purpose

Antiseptic

Use

Hand Sanitizer to help reduce bacteria that potentially can cause disease. For use when soap and water are not available.

Warnings

For external use only. Flammable. Keep away from heat or flame

Do not use

- in children less than 2 months of age
- on open skin wounds

When using this product keep out of eyes, ears, and mouth. In case of contact with eyes, rinse eyes thoroughly with water.
Stop use and ask a doctor if irritation and redness develops and persists.
Keep out of reach of children. If swallowed, get medical help or contact a Poison Control Center right away.

Stop use and ask a doctor if irritation or rash occurs. These may be signs of a serious condition.

Keep out of reach of children. If swallowed, get medical help or contact a Poison Control Center right away.

Directions

- Place enough product on hands to cover all surfaces. Rub hands together until dry.
- Supervise children under 6 years of age when using this product to avoid swallowing.

Other information

- Store between 15-30C (59-86F)
- Avoid freezing and excessive heat above 40C (104F)

Inactive ingredients

ACRYLATES/C10-30 ALKYL ACRYLATE CROSSPOLYMER, ALOE BARBADENSIS LEAF JUICE, AMINOMETHYL PROPANOL, CITRIC ACID, FRAGRANCE (PARFUM), GLYCERIN, HYDROXYPROPYL METHYLCELLULOSE, IRON OXIDES (CI 77492), MANNITOL, MICROCRYSTALLINE CELLULOSE, POTASSIUM SORBATE, SODIUM BENZOATE, TOCOPHERYL ACETATE, WATER (AQUA).

Package Label - Principal Display Panel

50 mL NDC: 72686-190-05